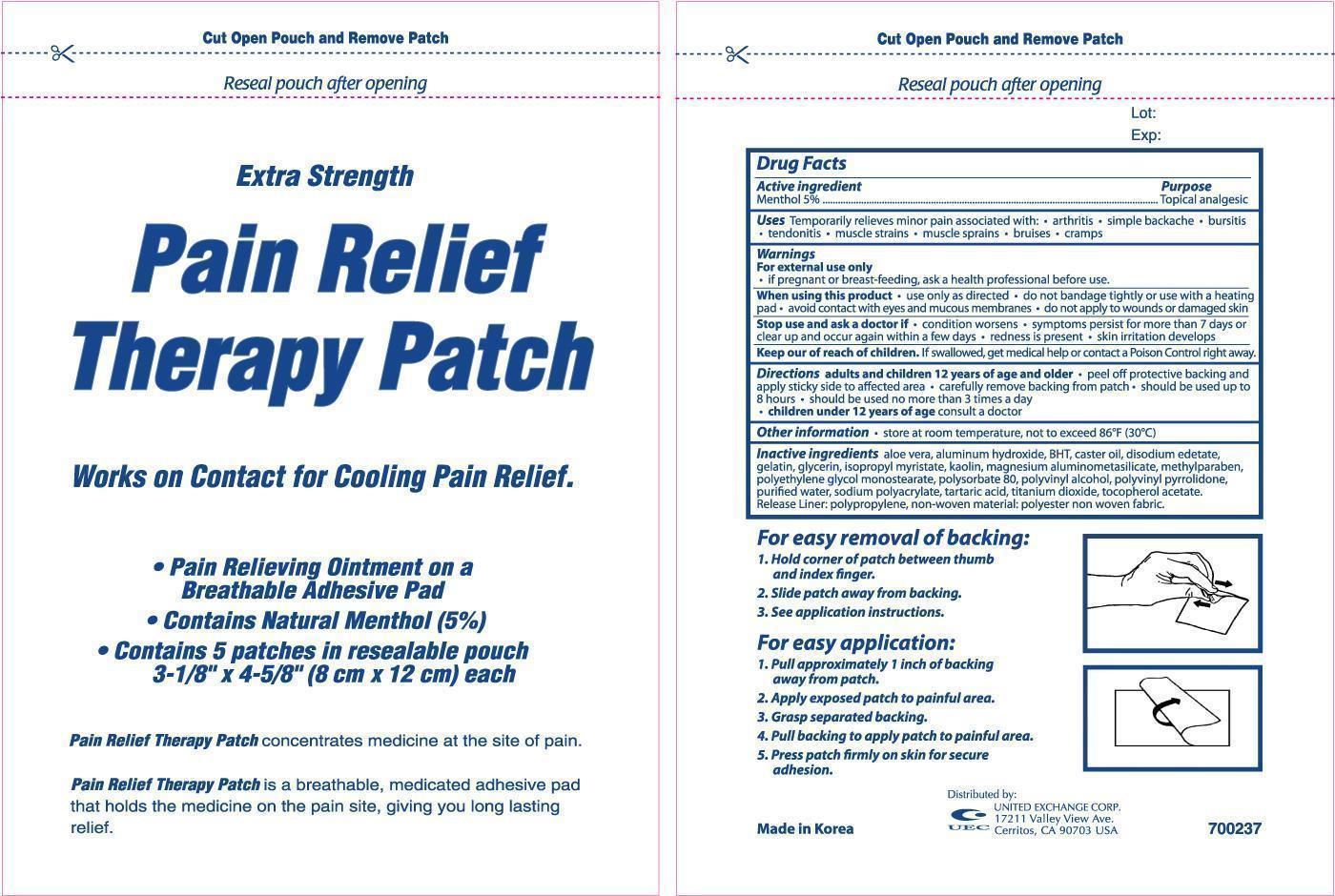 DRUG LABEL: Extra Strength Pain Relief Therapy
NDC: 65923-703 | Form: PATCH
Manufacturer: United Exchange Corp
Category: otc | Type: HUMAN OTC DRUG LABEL
Date: 20190916

ACTIVE INGREDIENTS: MENTHOL 750 mg/1 1
INACTIVE INGREDIENTS: BUTYLENE GLYCOL; EDETATE DISODIUM; GELATIN; GLYCERIN; KAOLIN; LIGHT MINERAL OIL; METHYLPARABEN; POLYSORBATE 80; WATER; SODIUM POLYMETAPHOSPHATE; SORBITAN MONOOLEATE; TARTARIC ACID; TITANIUM DIOXIDE; ALPHA-TOCOPHEROL ACETATE

Active ingredient Purpose

Menthol 5%.....................................................................Topical analgesic

PURPOSE

Uses Temporarily relieves minor pain associated with:

- arthritis
- simple backache
- bursitis
- tendonitis
- muscle strains
- muscle sprains
- bruises
- cramps

Warnings For external use only.

When using this product

- use only as directed
- do not bandage tightly or use with a heating pad
- avoid contact with eyes and mucous membranes
- do not apply to wounds or damaged skin

Stop use and ask a doctor if

- conditions worsen
- symptoms persist for more than 7 days or clear up and occur again within a few days
- redness is present
- skin irritation develops

Keep out of reach of children. If swallowed, get medical help or contact a Poison Control Center right away.

PREGNANCY OR BREAST FEEDING

If pregnant or breast-feeding, ask a health professional before use.

Directions

- adults and children 12 years of age and older
- peel off protective backing and apply sticky side to affected area
- carefully remove backing from patch
- should be used up to 8 hours
- should be used no more than 3 times a day
- children under 12 years of age consult a doctor

Other information

- store at room temperature, not to exceed 86°F (30° C)

INACTIVE INGREDIENT

Inactive ingredients 1,3-butylene glycol, aloe vera (powder), metacrylic acid butylacrylate copolymer, dibutylhydroxytoluene, disodium edetate, D-sorbitol solution, gelatin, glycerine, kaolin, light liquid paraffin, magnesium aluminium hydrate, methyl parahydroxybenzoate, polysorbate 80, purified water, sodium metaphosphate, sodium polyacrylate, sorbitan monooleate, tartaric acid, titanium oxide, tocopherol acetate.

DOSAGE AND ADMINISTRATION

Distributed By:

United Exchange Corp.

17211 Valley View Ave.

Cerritos, CA 90703 USA

Made in Korea